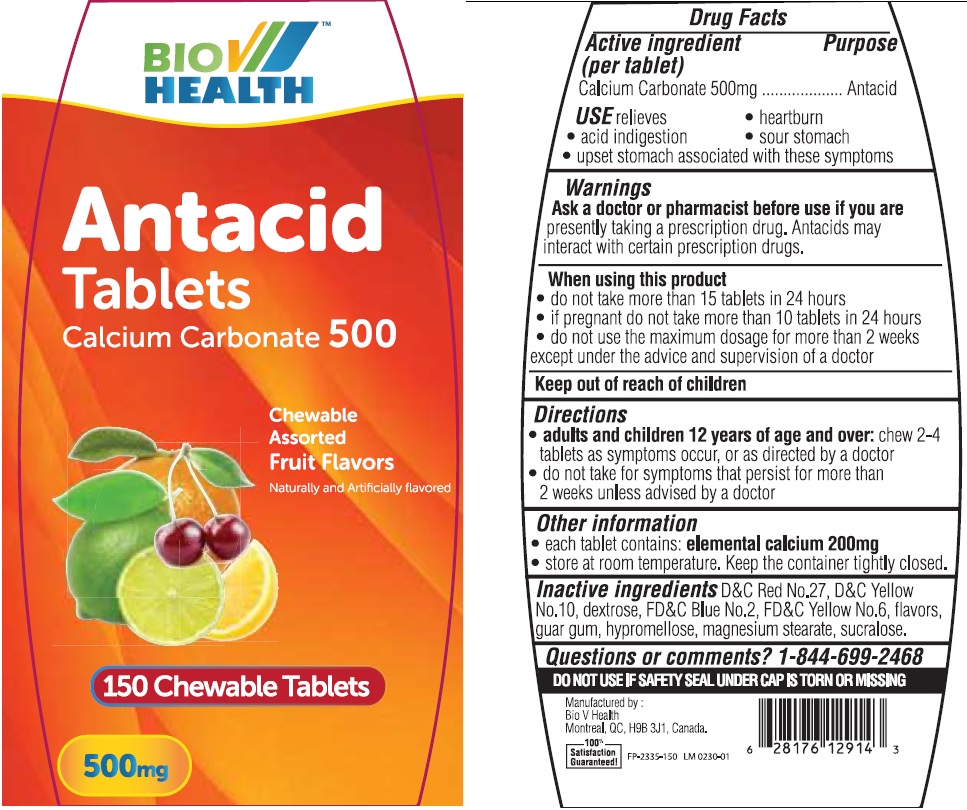 DRUG LABEL: Bio V Antacid Fruit Flavors
NDC: 71481-000 | Form: TABLET
Manufacturer: BioV Health Inc
Category: otc | Type: HUMAN OTC DRUG LABEL
Date: 20211222

ACTIVE INGREDIENTS: CALCIUM CARBONATE 500 mg/1 1
INACTIVE INGREDIENTS: D&C RED NO. 27; D&C YELLOW NO. 10; DEXTROSE; FD&C BLUE NO. 2; FD&C YELLOW NO. 6; METHYL SALICYLATE; GUAR GUM; HYPROMELLOSE, UNSPECIFIED; MAGNESIUM STEARATE; SUCRALOSE

Bio V Antacid Tablets Fruit Flavors

Active ingredient (per tablet)

Calcium Carbonate 500mg

Purpose

Antacid

USE

relieves

• heartburn • acid indigestion • sour stomach • upset stomach associated with these symptoms

Warnings

Ask a doctor or pharmacist before use if you are

presently taking a prescription drug. Antacids may interact with certain prescription drugs.

When using this product

- do not take more than 15 tablets in 24 hours
- if pregnant do not take more than 10 tablets in 24 hours
- do not use the maximum dosage for more than 2 weeks except under the adive and supervision of a doctor

Directions

- adults and children 12 years of age and over: chew 2-4 tablets as symptoms occur, or as directed by a doctor
- do not take for symptoms that persist for more than 2 weeks unless advised by a doctor

Other information

- each tablet contains: elemental calcium 200mg
- store at room temperature. Keep the container tightly closed.

Inactive ingredients

D&C Red No.27, D&C Yellow No. 10, dextrose, FD&C Blue No.2, FD&C Yellow No.6, flavors, guar gum, hypromellose, magnesium stearate, sucralose.

Questions or comments?

1-844-699-2468